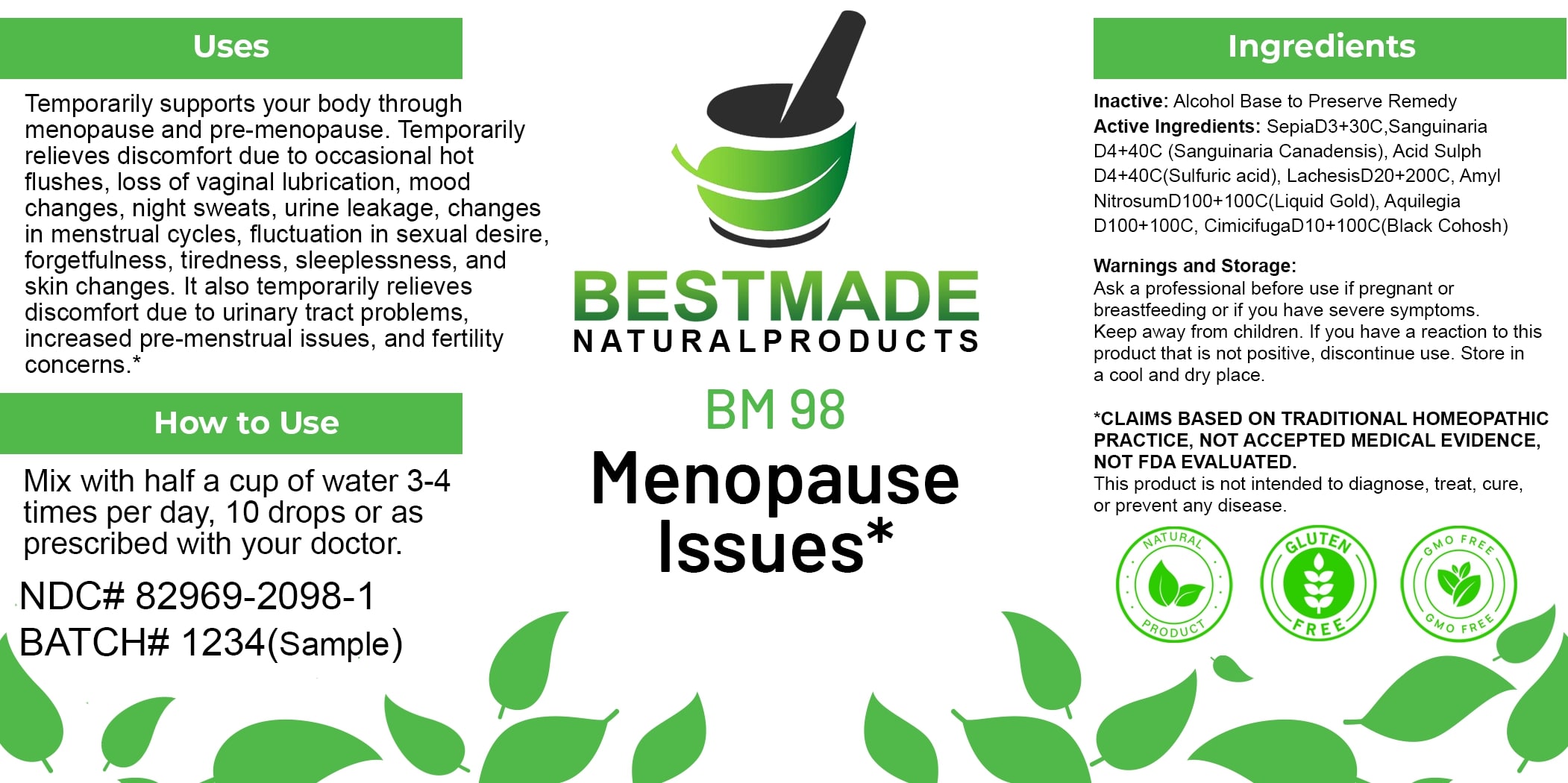 DRUG LABEL: Bestmade Natural Products BM98
NDC: 82969-2098 | Form: LIQUID
Manufacturer: Bestmade Natural Products
Category: homeopathic | Type: HUMAN OTC DRUG LABEL
Date: 20250205

ACTIVE INGREDIENTS: CIMICIFUGA RACEMOSA ROOT 30 [hp_C]/30 [hp_C]; AMYL NITRITE 30 [hp_C]/30 [hp_C]; LACHESIS MUTA VENOM 30 [hp_C]/30 [hp_C]; SEPIA OFFICINALIS JUICE 30 [hp_C]/30 [hp_C]; SANGUINARIA CANADENSIS ROOT 30 [hp_C]/30 [hp_C]; SULFURIC ACID 30 [hp_C]/30 [hp_C]; AQUILEGIA VULGARIS 30 [hp_C]/30 [hp_C]
INACTIVE INGREDIENTS: ALCOHOL 30 [hp_C]/30 [hp_C]

BM98

DOSAGE AND ADMINISTRATION

How to Use

Mix with half a cup of water 3-4 times per day, 10 drops or as prescribed with your doctor.

INACTIVE INGREDIENT

Ingredients

Inactive: Alcohol Base to Preserve Remedy

ACTIVE INGREDIENT

Active Ingredients: Sepia D3+30C, Sanguinaria D4+40C (Sanguinaria Canadensis), Acid Sulph D4+40C (Sulfuric acid), Lachesis D20+200C, Amyl Nitrosum D100+100C (Liquid Gold), Aquilegia D100+100C, Cimicifuga D10+100C (Black Cohosh)

Uses

Temporarily supports your body through menopause and pre-menopause. Temporarily relieves discomfort due to occasional hot flushes, loss of vaginal lubrication, mood changes, night sweats, urine leakage, changes in menstrual cycles, fluctuation in sexual desire, forgetfulness, tiredness, sleeplessness, and skin changes. It also temporarily relieves discomfort due to urinary tract problems, increased pre-menstrual issues, and fertility concerns.*

*CLAIMS BASED ON TRADITIONAL HOMEOPATHIC PRACTICE, NOT ACCEPTED MEDICAL EVIDENCE. NOT FDA EVALUATED.

This product is not intended to diagnose, treat, cure, or prevent any disease.

Uses

Temporarily supports your body through menopause and pre-menopause. Temporarily relieves discomfort due to occasional hot flushes, loss of vaginal lubrication, mood changes, night sweats, urine leakage, changes in menstrual cycles, fluctuation in sexual desire, forgetfulness, tiredness, sleeplessness, and skin changes. It also temporarily relieves discomfort due to urinary tract problems, increased pre-menstrual issues, and fertility concerns.*

*CLAIMS BASED ON TRADITIONAL HOMEOPATHIC PRACTICE, NOT ACCEPTED MEDICAL EVIDENCE. NOT FDA EVALUATED.

This product is not intended to diagnose, treat, cure, or prevent any disease.

KEEP OUT OF REACH OF CHILDREN

Warnings and Storage:

Ask a professional before use if pregnant or breastfeeding or if you have severe symptoms. Keep away from children. If you have a reaction to this product that is not positive, discontinue use. Store in a cool and dry place.

Warnings and Storage:

Ask a professional before use if pregnant or breastfeeding or if you have severe symptoms. Keep away from children. If you have a reaction to this product that is not positive, discontinue use. Store in a cool and dry place.

*CLAIMS BASED ON TRADITIONAL HOMEOPATHIC PRACTICE, NOT ACCEPTED MEDICAL EVIDENCE. NOT FDA EVALUATED.

This product is not intended to diagnose, treat, cure, or prevent any disease.

Entire package label